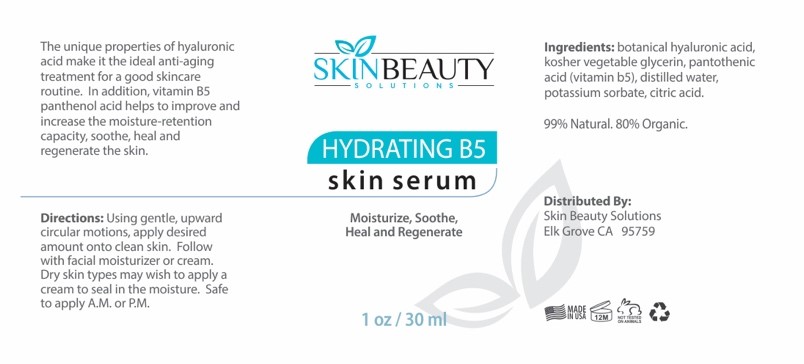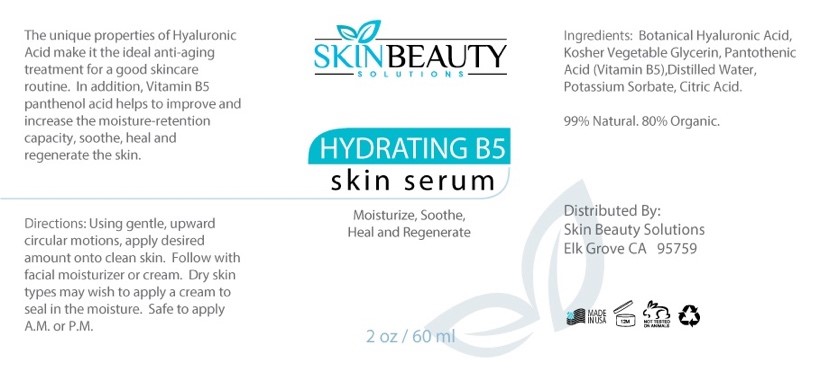 DRUG LABEL: Hydrating B5 serum
NDC: 84785-0009 | Form: SOLUTION
Manufacturer: Gazebo Wellness SKIN LLC
Category: otc | Type: HUMAN OTC DRUG LABEL
Date: 20241216

ACTIVE INGREDIENTS: HYALURONIC ACID 0.3 mg/30 mL; PANTOTHENIC ACID 0.3 mg/30 mL
INACTIVE INGREDIENTS: WATER; POTASSIUM SORBATE; CITRIC ACID ACETATE; GLYCERIN

DOSAGE AND ADMINISTRATION

The unique properties of hyaluronic acid make it the ideal anti-aging treatment for a good skincare routine. In addition, vitamin B5 panthenol acid helps to improve and increase the moisture-retention capacity, soothe, heal and regenerate the skin.

WARNINGS

Using gentle, upward circular motions, apply desired amount onto clean skin. Follow with facial moisturizer or cream. Dry skin types may wish to apply a cream to seal in the moisture. Safe to apply A.M. or PM.

INACTIVE INGREDIENT

Inactive ingredients: Kosher Vegetable Glycerin, Distilled Water, Potassium Sorbate, Citric Acid.

ACTIVE INGREDIENT

Active ingredients: Botanical Hyaluronic Acid, Pantothenic Acid (Vitamin B5).

INDICATIONS AND USAGE

Directions: Using gentle, upward circular motions, apply desired amount onto clean skin. Follow with facial moisturizer or cream. Dry skin types may wish to apply a cream to seal in the moisture. Safe to apply A.M. or PM.

keep out of reach of children

PURPOSE

HYDRATING B5 skin serum
Moisturize, Soothe, Heal and Regenerate

Distributed By:
Skin Beauty Solutions Elk Grove CA 95759

PACKAGE LABEL

Content of labeling